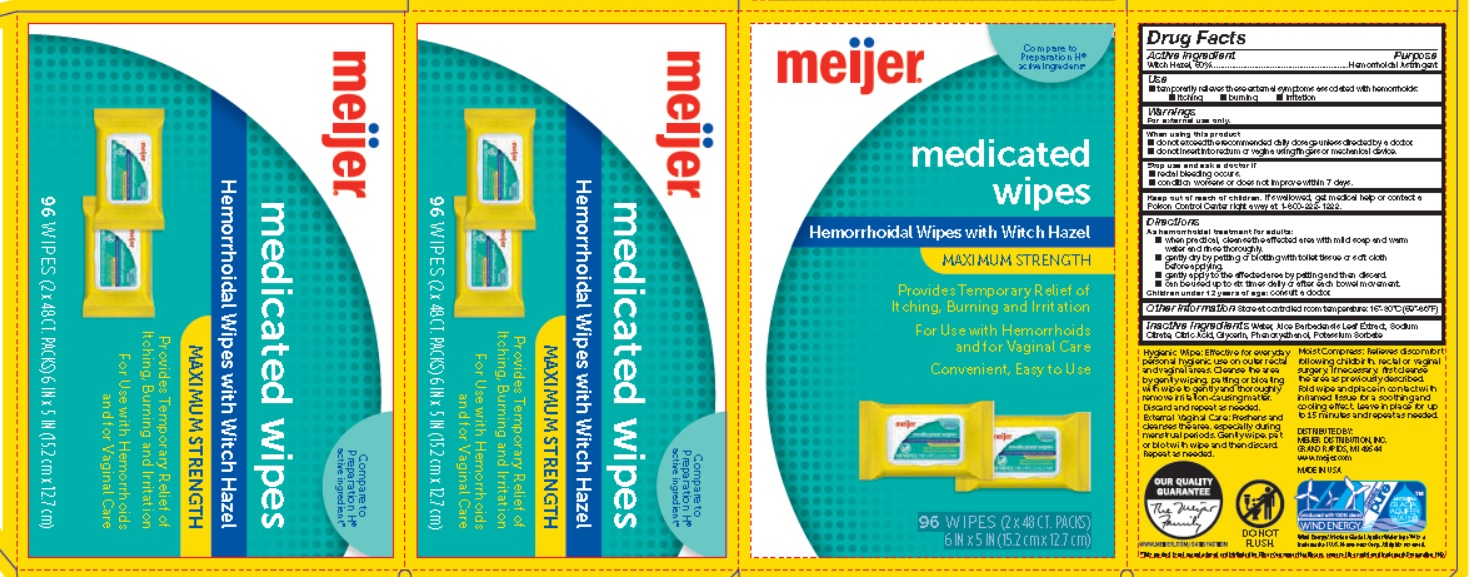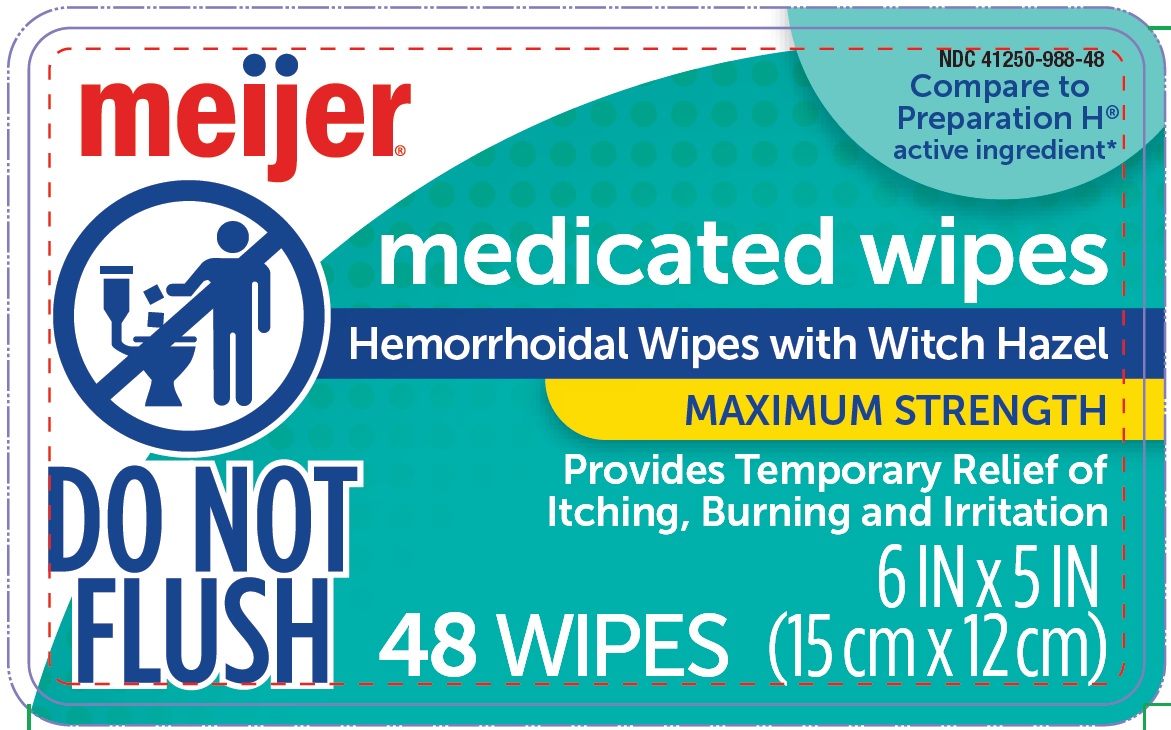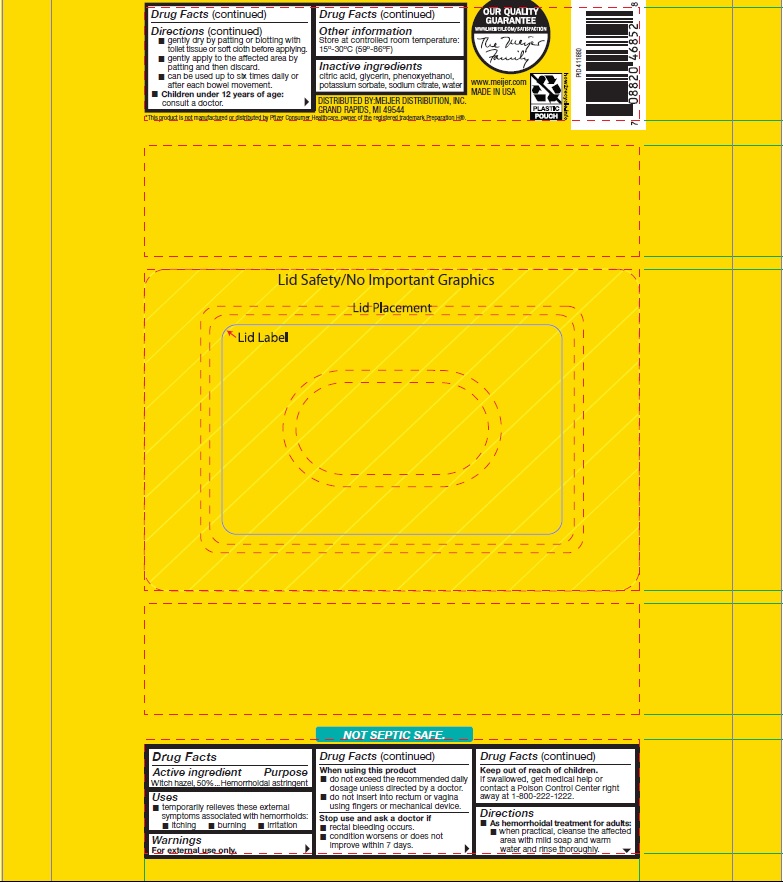 DRUG LABEL: medicated wipes
NDC: 41250-988 | Form: PATCH
Manufacturer: Meijer Distribution Inc.
Category: otc | Type: HUMAN OTC DRUG LABEL
Date: 20250711

ACTIVE INGREDIENTS: WITCH HAZEL 500 mg/1000 mg
INACTIVE INGREDIENTS: WATER; SODIUM CITRATE; CITRIC ACID MONOHYDRATE; GLYCERIN; PHENOXYETHANOL; POTASSIUM SORBATE

Drug Facts

Active Ingredient

Witch Hazel 50%

Purpose

Hemorrhoidal Astringent

Uses

Temporarily relieves these external symptoms associated with hemorrhoids:

- itching
- burning
- irritation

Warnings

For external rectal use only.

When using this product

- do not exceed the recommended daily dosage unless directed by a doctor.
- do not insert into rectum or vagina using fingers or mechanical device.

Stop use and ask a doctor if

- rectal bleeding occurs
- condition worsens or does not improve within 7 days.

Keep out of reach of children.

If swallowed, get medical help or contact a Poison Control Center right away at 1-800-222-1222.

Directions

As hemorrhoidal treatment for adults:

- when practical, cleanse the affected area with mild soap and warm water and rinse thoroughly.
- gently dry by patting or blotting with toilet tissue or soft cloth before applying.
- gently apply to the affected area by patting and then discard.
- can be used up to six times daily or after each bowel movement.

Children under 12 years of age

- consult a doctor.

Other Information

Store at controlled room temperature: 15º-30ºC (59º-86ºF)

Inactive Ingredients

Water, Sodium citrate, Citric acid, Glycerin, Phenoxyethanol, Potassium sorbate

Principal Display Panel

NDC 41250-988-48

meijer

Compare to Preparation H® active ingredient*

medicated wipes

Hemorrhoidal Wipes with Witch Hazel

MAXIMUM STRENGTH

Provides Temporary Relief of Itching, Burning and Irritation
48 WIPES
6 IN x 5 IN (15cm x 12cm)

NDC 41250-988-96

meijer

Compare to Preparation H® active ingredient*

medicated wipes

Hemorrhoidal Wipes with Witch Hazel

MAXIMUM STRENGTH

Provides Temporary Relief of Itching, Burning and Irritation
For Use with Hemorrhoids and for Vaginal Care
Convenient, Easy to Use

96 WIPES (2 x 48 CT. PACKS)
6 IN x 5 IN (15.2 cm x 12.7 cm)